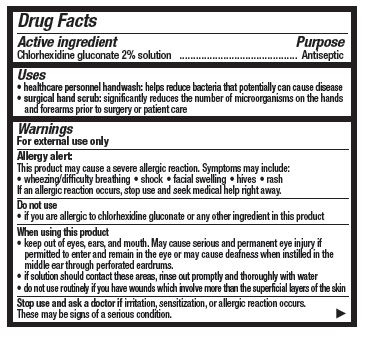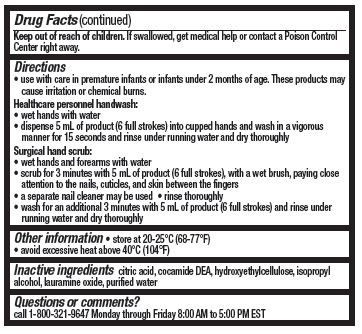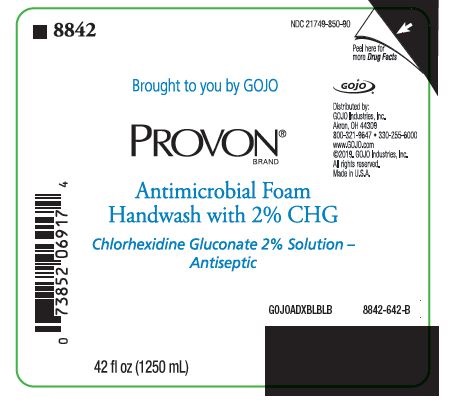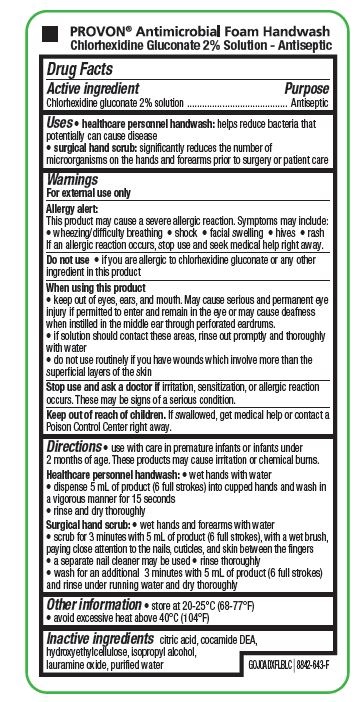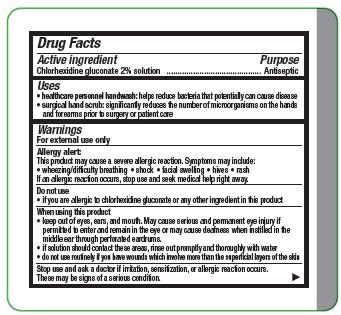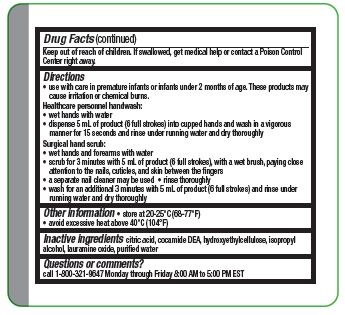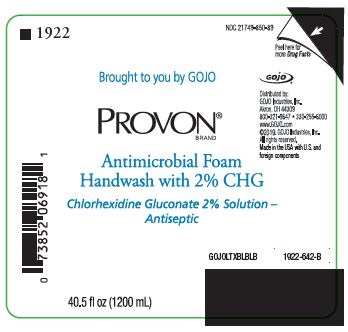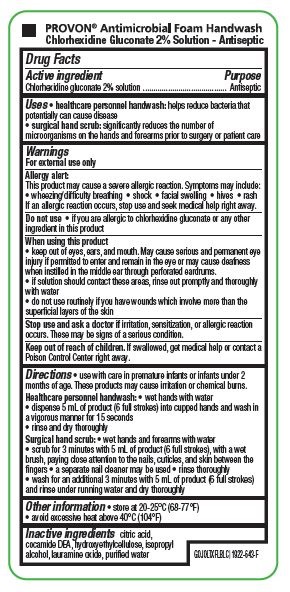 DRUG LABEL: Provon Antimicrobial Foam Handwash
NDC: 0116-8500 | Form: SOLUTION
Manufacturer: Xttrium Laboratories, Inc.
Category: otc | Type: HUMAN OTC DRUG LABEL
Date: 20250430

ACTIVE INGREDIENTS: CHLORHEXIDINE GLUCONATE 20 mg/1 mL
INACTIVE INGREDIENTS: CITRIC ACID MONOHYDRATE; COCO DIETHANOLAMIDE; HYDROXYETHYL CELLULOSE (2000 MPA.S AT 1%); ISOPROPYL ALCOHOL; LAURAMINE OXIDE; WATER

2% GOJO ADX/LTX

Active ingredient

chlorhexidine gluconate 2% solution

Purpose

Antiseptic

Uses

- healthcare personnel handwash: helps reduce bacteria that potentially can cause disease
- surgical hand scrub: significantly reduces the number of microorganisms on the hands and forearms prior to surgery or patient care

Warnings

For external use only

Allergy alert:

This product may cause a severe allergic reaction. Symptoms may include:

• wheezing/difficulty breathing

• shock

• facial swelling

• hives

• rash

If an allergic reaction occurs, stop use and seek medical help right away.

Do not use

- if you are allergic to chlorhexidine gluconate or any other ingredient in this product

When using this product

- keep out of eyes, ears, and mouth. May cause serious and permanent eye injury if permitted to enter and remain in the eye or may cause deafness when instilled in the middle ear through perforated eardrums.
- if solution should contact these areas, rinse out promptly and thoroughly with water
- do not use routinely if you have wounds which involve more than the superficial layers of the skin

Stop use and ask a doctor if irritation, sensitization or allergic reaction occurs. These may be signs of a serious condition.

Keep out of reach of children. If swallowed, get medical help or contact a Poison Control Center right away.

Directions

- Use with care in premature infants or infants under 2 months of age. These products may cause irritation or chemical burns.

Healthcare personnel handwash:

- wet hands with water
- dispense 5 mL of product (6 full strokes) into cupped hands and wash in a vigorous manner for 15 seconds and rinse under running water and dry thoroughly

Surgical hand scrub:

- wet hands and forearms with water
- scrub for 3 minutes with 5 mL of product (6 full stokes), with a wet brush, paying close attention to the nails, cuticles, and skin between the fingers
- a seperate nail cleaner may be used
- rinse thoroughly
- wash for an additional 3 minutes with 5 mL of product (6 full strokes) and rinse under running water and dry thoroughly

Other information

- store at 20-25° C (68-77° F)
- avoid excessive heat above 40° C (104° F)

Inactive ingredients

citric add. cocamide DEA, hydroxyethylcellulose, isopropyl alcohol, lauramine oxide, purified water

Questions or comments?

call 1-800-321-9647 Monday through Friday 8:00 AM to 5:00 PM EST

RECENT MAJOR CHANGES

Indications and Usage

Dosage and Administration

PACKAGE LABEL

PROVON® Antimicrobial Foam Handwash

Chlorhexidine Gluconate 2% Solution - Antiseptic

GOJOADXFLBLC

8842-643-F

8842

NDC 21749-850-90

Brought to you by GOJO

PROVON®

Antimicrobial Foam Handwash with 2% CHG

Chlorhexidine Gluconate 2% Solution - Antiseptic

42 fl oz (1250 mL)

GOJOADXBLBLB

8842-642-B

PROVON® Antimicrobial Foam Handwash

Chlorhexidine Gluconate 2% Solution - Antiseptic

GOJOLTXFLBLC

1922-643-F

.

1922

NDC 21749-850-89

Brought to you by GOJO

PROVON®

Antimicrobial Foam Handwash with 2% CHG

Chlorhexidine Gluconate 2% Solution - Antiseptic

40.5 fl oz (1200 mL)

GOJOLTXBLBLB

1922-642-B